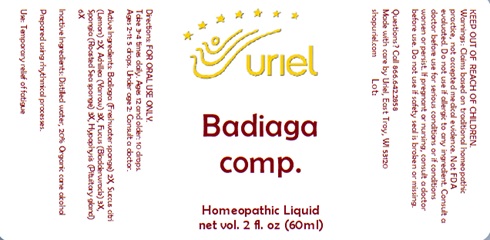 DRUG LABEL: Badiaga comp.
NDC: 48951-2152 | Form: LIQUID
Manufacturer: Uriel Pharmacy, Inc.
Category: homeopathic | Type: HUMAN OTC DRUG LABEL
Date: 20240621

ACTIVE INGREDIENTS: FUCUS VESICULOSUS 3 [hp_X]/1 mL; BOS TAURUS PITUITARY GLAND 6 [hp_X]/1 mL; SPONGILLA LACUSTRIS 2 [hp_X]/1 mL; CITRUS RETICULATA FRUIT OIL 2 [hp_X]/1 mL; ACHILLEA MILLEFOLIUM 3 [hp_X]/1 mL; SPONGIA OFFICINALIS SKELETON, ROASTED 3 [hp_X]/1 mL
INACTIVE INGREDIENTS: ALCOHOL; WATER

Badiaga comp.

INDICATIONS AND USAGE

Directions: FOR ORAL USE ONLY.

DOSAGE AND ADMINISTRATION

Take 3-4 times daily. Ages 12 and older: 10 drops.
Ages 2-11: 5 drops. Under age 2: Consult a doctor.

ACTIVE INGREDIENT

Active Ingredients: Badiaga (Freshwater sponge) 2X, Succus citri (Lemon) 2X, Achillea (Yarrow) 3X, Fucus (Bladderwrack) 3X, Spongia (Roasted Sea sponge) 3X, Hypophysis (Pituitary gland) 6X (1 : 1 : 1 : 2 : 1 : 2)

Inactive Ingredients: Distilled water, 20% Organic cane alcohol
Prepared using rhythmical processes.

PURPOSE

Use: Temporary relief of fatigue

KEEP OUT OF REACH OF CHILDREN.

WARNINGS

Warnings: Claims based on traditional homeopathic practice, not accepted medical evidence. Not FDA evaluated. Do not use if allergic to any ingredient. Consult a doctor before use for serious conditions or if conditions worsen or persist. If pregnant or nursing, consult a doctor before use. Do not use if safety seal is broken or missing.

Questions? Call 866.642.2858
Made with care by Uriel, East Troy, WI 53120
shopuriel.com Lot: